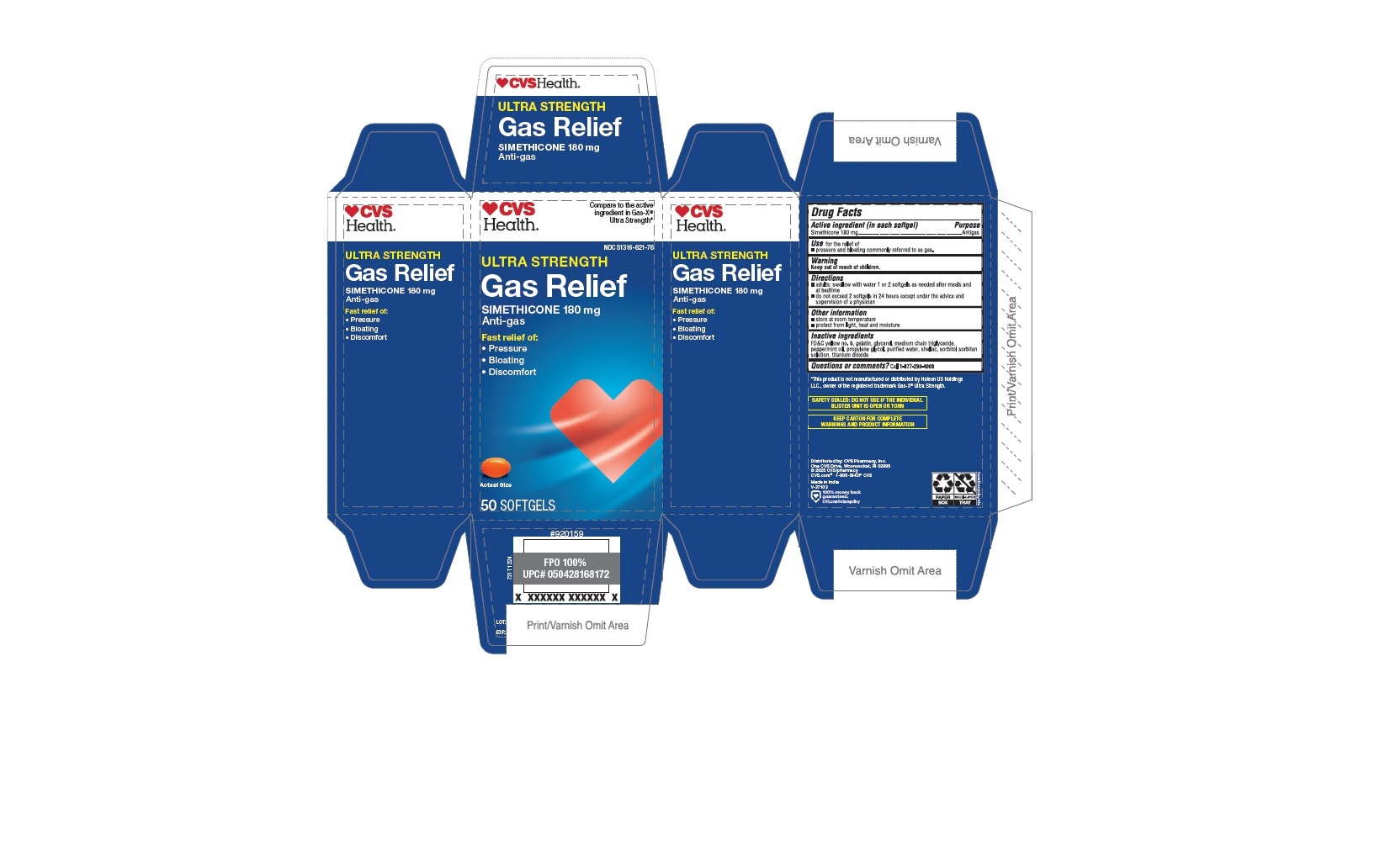 DRUG LABEL: Ultrastrength Gas Relief
NDC: 51316-621 | Form: CAPSULE
Manufacturer: CVS PHARMACY, INC
Category: otc | Type: HUMAN OTC DRUG LABEL
Date: 20250129

ACTIVE INGREDIENTS: DIMETHICONE 180 mg/1 1
INACTIVE INGREDIENTS: SHELLAC; GLYCERIN; PEPPERMINT OIL; SORBITAN; FD&C YELLOW NO. 6; MEDIUM-CHAIN TRIGLYCERIDES; SORBITOL; WATER; PROPYLENE GLYCOL; TITANIUM DIOXIDE; GELATIN

CVS_721T_51316-621_Simethicone Soft Gelatin Capsules 180 mg

Active ingredient (in each softgel)

Simethicone 180 mg

Purpose

Anti-gas

INDICATIONS AND USAGE

Use for the relief of

- pressure and bloating commonly referred to as gas.

Warning

Keep out of reach of children.

Directions

- adults: swallow with water 1 or 2 softgels as needed after meals and at bedtime
- do not exceed 2 softgels in 24 hours except under the advice and supervision of a physician

Other information

- store at room temperature
- protect from light, heat and moisture

Inactive ingredients

FD&C yellow no. 6, gelatin, glycerol, medium chain triglyceride, peppermint oil, propylene glycol, purified water, shellac, sorbitol sorbitan solution, titanium dioxide

Questions or comments? Call 1-877-290-4008